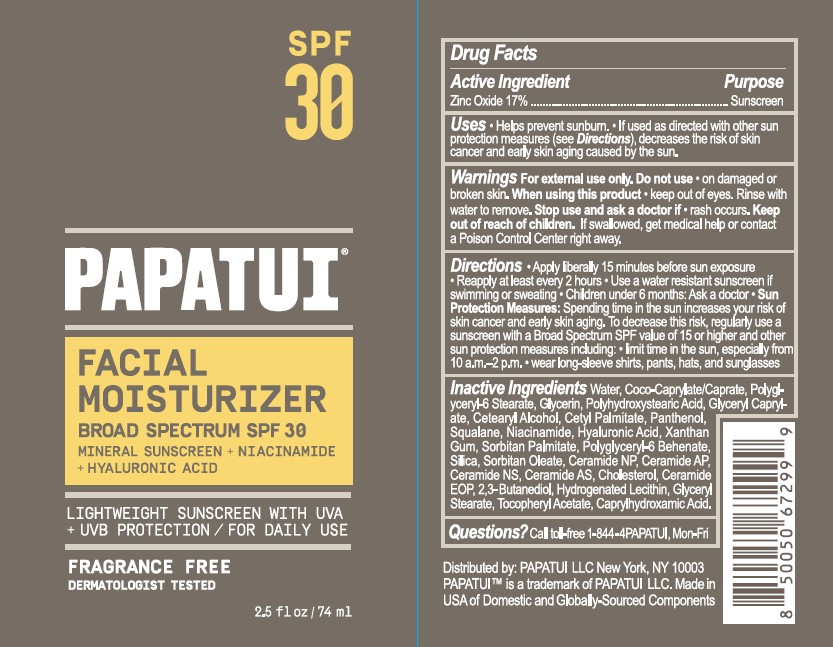 DRUG LABEL: PAPATUI Facial Moisturizer Broad Spectrum SPF 30
NDC: 83850-300 | Form: CREAM
Manufacturer: PAPATUI, LLC
Category: otc | Type: HUMAN OTC DRUG LABEL
Date: 20250826

ACTIVE INGREDIENTS: ZINC OXIDE 17 g/100 mL
INACTIVE INGREDIENTS: HYDROGENATED SOYBEAN LECITHIN; COCO-CAPRYLATE/CAPRATE; ALPHA-TOCOPHEROL ACETATE; WATER; POLYGLYCERYL-6 STEARATE; CETEARYL ALCOHOL; SQUALANE; GLYCERYL STEARATE; SORBITAN PALMITATE; GLYCERIN; GLYCERYL CAPRYLATE; HYALURONIC ACID; SILICON DIOXIDE; PANTHENOL; CERAMIDE AP; CHOLESTEROL; POLYHYDROXYSTEARIC ACID (2300 MW); SORBITAN OLEATE; CERAMIDE NS; CERAMIDE 9; CETYL PALMITATE; POLYGLYCERYL-6 BEHENATE; CERAMIDE NP; CERAMIDE 5; CAPRYLHYDROXAMIC ACID; NIACINAMIDE; XANTHAN GUM; 2,3-BUTANEDIOL

PAPATUI Facial Moisturizer Broad Spectrum SPF 30

Drug Facts

Active Ingredient

Active Ingredient | Purpose
Zinc Oxide 17% | Sunscreen

Uses

- Helps prevent sunburn.
- If used as directed with other sun protection measures (see Directions), decreases the risk of skin cancer and early skin aging caused by the sun.

Warnings

For external use only.

Do not use

- On damaged or broken skin.

When using this product

- keep out of eyes. Rinse with water to remove.

Stop use and ask a doctor if

- rash occurs.

Keep out of reach of children. If swallowed, get medical help or contact a Poison Control Center right away.

Directions

- Apply liberally 15 minutes before sun exposure
- Reapply at least every 2 hours
- Use a water resistant sunscreen if swimming or sweating
- Children under 6 months: Ask a doctor
- Sun Protection Measures: Spending time in the sun increases your risk of skin cancer and early skin aging. To decrease this risk, regularly use a sunscreen with a Broad Spectrum SPF value of 15 or higher and other sun protection measures including:
- limit time in the sun, especially from 10 a.m.-2 p.m.
- Wear long-sleeve shirts, pants, hats, and sunglasses

Inactive Ingredients

Water, Coco-Caprylate/Caprate, Polyglyceryl-6 Stearate, Glycerin, Polyhydroxystearic Acid, Glyceryl Caprylate, Cetearyl Alcohol, Cetyl Palmitate, Panthenol, Squalane, Niacinamide, Hyaluronic Acid, Xanthan Gum, Sorbitan Palmitate, Polyglyceryl-6 Behenate, Silica, Sorbitan Oleate, Ceramide NP, Ceramide AP, Ceramide NS, Ceramide AS, Cholesterol, Ceramide EOP, 2,3-Butanediol, Hydrogenated Lecithin, Glyceryl Stearate, Tocopheryl Acetate, Caprylhydroxamic Acid.

Questions?

Questions? Call toll-free 1-844-4PAPATUI, Mon-Fri

PRINCIPAL DISPLAY PANEL - 74 mL Tube

PAPATUI

Facial

Mosturizer

Broad Spectrum SPF 30

Mineral Sunscreen + Niacinamide

+ Hyaluronic Acid

Lightweight Sunscreen with UVA

+ UVB Protection / For Daily Use

Fragrance Free

Dermatologist Tested

2.5 fl oz / 74 ml